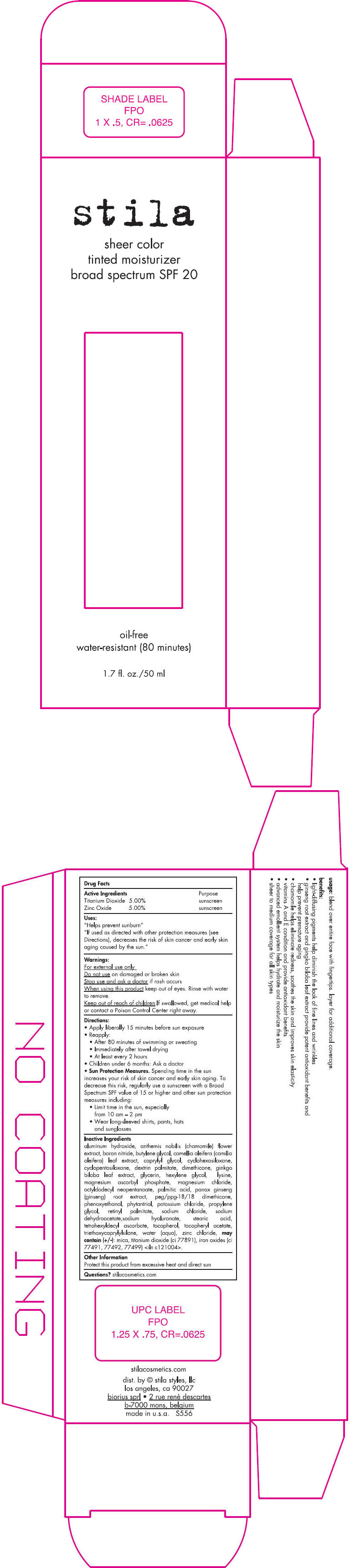 DRUG LABEL: Stila Sheer color tinted moisturizer BS SPF20 
NDC: 76049-556 | Form: LOTION
Manufacturer: Stila Styles, LLC
Category: otc | Type: HUMAN OTC DRUG LABEL
Date: 20131122

ACTIVE INGREDIENTS: Titanium Dioxide 50 mg/1 mL; Zinc Oxide 50 mg/1 mL
INACTIVE INGREDIENTS: aluminum hydroxide; chamaemelum nobile flower; boron nitride; butylene glycol; camellia oleifera leaf; caprylyl glycol; cyclomethicone 6; cyclomethicone 5; dimethicone; ginkgo; glycerin; hexylene glycol; lysine; magnesium ascorbyl phosphate; magnesium chloride; octyldodecyl neopentanoate; palmitic acid; asian ginseng; peg/ppg-18/18 dimethicone; phenoxyethanol; phytantriol; potassium chloride; propylene glycol; vitamin a palmitate; sodium chloride; sodium dehydroacetate; hyaluronate sodium; stearic acid; tetrahexyldecyl ascorbate; tocopherol; .alpha.-tocopherol acetate; triethoxycaprylylsilane; water; zinc chloride; mica; ferric oxide red; ferric oxide yellow; ferrosoferric oxide

Stila Sheer color tinted moisturizer broad spectrum SPF 20
(All Shades)

Drug Facts

ACTIVE INGREDIENT

Active Ingredients | Purpose
Titanium Dioxide 5.00% | sunscreen
Zinc Oxide 5.00% | sunscreen

Uses

"Helps prevent sunburn"

"If used as directed with other protection measures (see Directions), decreases the risk of skin cancer and early skin aging caused by the sun."

Warnings

For external use only

Do not use on damaged or broken skin

Stop use and ask a doctor if rash occurs

When using this product keep out of eyes. Rinse with water to remove.

Keep out of reach of children.If swallowed, get medical help or contact a Poison Control Center right away.

Directions

- Apply liberally 15 minutes before sun exposure
- Reapply:
  - After 80 minutes of swimming or sweating
  - Immediately after towel drying
  - At least every 2 hours
- Children under 6 months: Ask a doctor
- Sun Protection Measures. Spending time in the sun increases your risk of skin cancer and early skin aging. To decrease this risk, regularly use a sunscreen with a Broad Spectrum SPF value of 15 or higher and other sun protection measures including:
  - Limit time in the sun, especially from 10 am – 2 pm
  - Wear long-sleeved shirts, pants, hats and sunglasses

Inactive Ingredients

aluminum hydroxide, anthemis nobilis (chamomile) flower extract, boron nitride, butylene glycol, camellia oleifera (camilia oleifera) leaf extract, caprylyl glycol, cyclohexasiloxane, cyclopentasiloxane, dextrin palmitate, dimethicone, ginkgo biloba leaf extract, glycerin, hexylene glycol, lysine, magnesium ascorbyl phosphate, magnesium chloride, octyldodecyl neopentanoate, palmitic acid, panax ginseng (ginseng) root extract, peg/ppg-18/18 dimethicone, phenoxyethanol, phytantriol, potassium chloride, propylene glycol, retinyl palmitate, sodium chloride, sodium dehydroacetate,sodium hyaluronate, stearic acid, tetrahexyldecyl ascorbate, tocopherol, tocopheryl acetate, triethoxycaprylylsilane, water (aqua), zinc chloride, may contain (+\-): mica, titanium dioxide (ci 77891), iron oxides (ci 77491, 77492, 77499) <iln c121004>.

Other Information

Protect this product from excessive heat and direct sun

Questions?

stilacosmetics.com

dist. by stila styles, llc
los angeles, ca 90027

PRINCIPAL DISPLAY PANEL - 50 ml Tube Carton

stila

sheer color
tinted moisturizer
broad spectrum SPF 20

oil-free
water-resistant (80 minutes)

1.7 fl. oz./50 ml